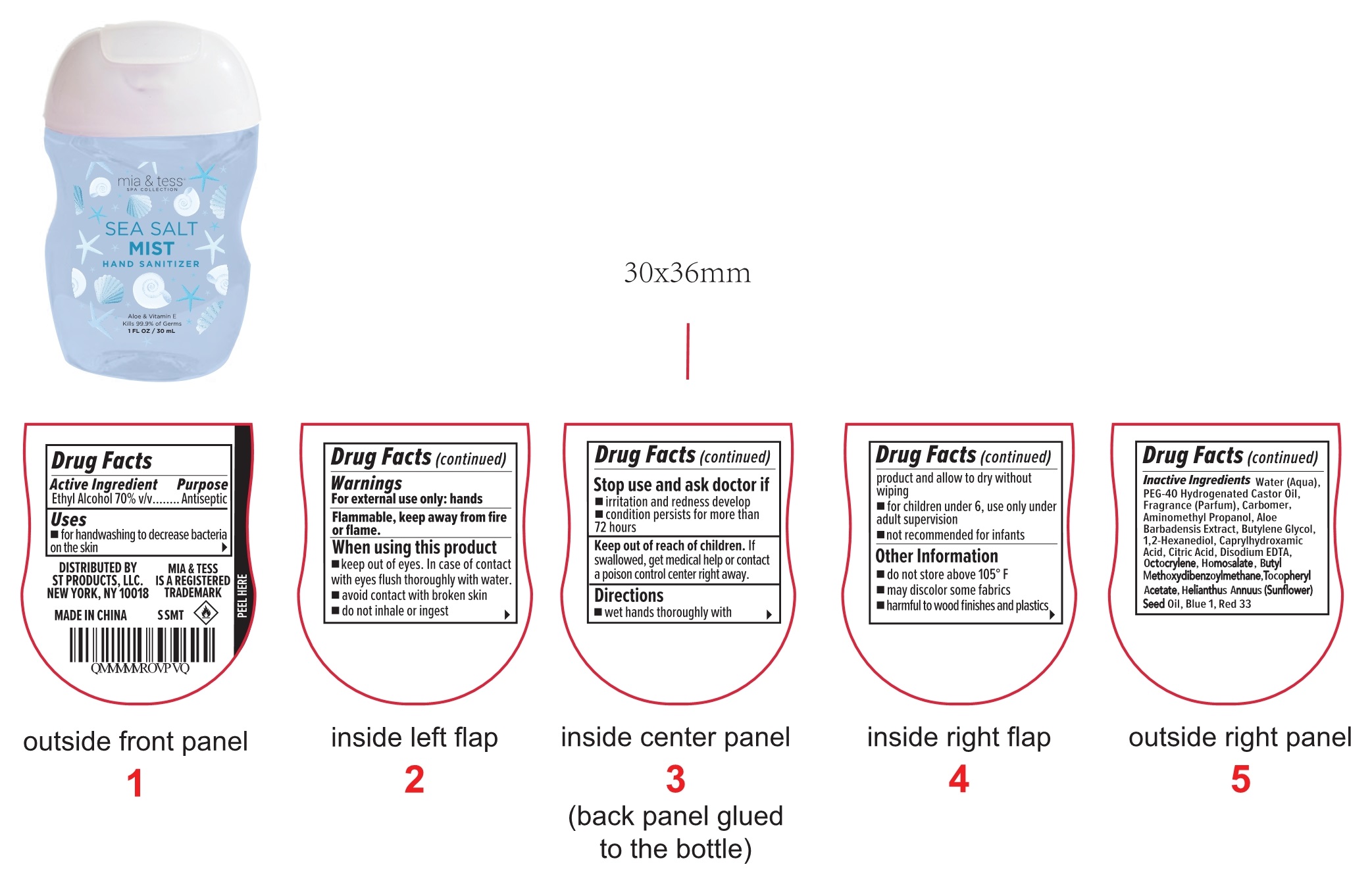 DRUG LABEL: HAND SANITIZER
NDC: 73549-027 | Form: LIQUID
Manufacturer: Fortress Expert Co., Ltd
Category: otc | Type: HUMAN OTC DRUG LABEL
Date: 20210714

ACTIVE INGREDIENTS: ALCOHOL 70 mL/100 mL
INACTIVE INGREDIENTS: BUTYLENE GLYCOL; CAPRYLHYDROXAMIC ACID; EDETATE DISODIUM ANHYDROUS; ALOE VERA WHOLE; FD&C BLUE NO. 1; .ALPHA.-TOCOPHEROL ACETATE; FRAGRANCE FLORAL ORC0902236; WATER; CARBOMER INTERPOLYMER TYPE A (ALLYL SUCROSE CROSSLINKED); AMINOMETHYLPROPANOL; POLYOXYL 40 HYDROGENATED CASTOR OIL; 1,2-HEXANEDIOL; CITRIC ACID MONOHYDRATE; D&C RED NO. 33; OCTOCRYLENE; AVOBENZONE; HOMOSALATE; SUNFLOWER OIL

73549-027
HAND SANITIZER

Active ingredient

Ethyl Alcohol 70%

Purpose

Antiseptic

Use

■For handwashing to decrease bacteria on the skin.

Warnings

For external use only: hands
Flammable, keep away from fire or flame

When using this product

■keep out of eyes.In case of contact with eyes flush thoroughly with water.
■avoid contact with broken skin
■do not inhale or ingest

Stop use and ask a doctor if

■irritation and redness develop
■condition persists for more than 72 hours

Keep out of reach of children.If swallowed, get medical help or contact a poison control center right away.

Directions

■wet hands thoroughly with product and allow to dry without wiping
■for children under 6, use only under adult supervision
■not recommended for infants

Other information

■do not store above 105°F
■may discolor some fabrics
■harmful to wood finishes and plastics

Inactive ingredients

Water(Aqua), PEG-40 Hydrogenated Castor Oil, Fragrance(Parfum) , Acrylates/ C10-30Alkyl Acrylate Crosspolymer, Aminomethyl Propanol, Aloe Barbadensis Extract, Butylene Glycol, 1,2-Hexanediol, Caprylhydroxamic Acid, Citric Acid, Disodium EDTA, Octocrylene, Homosalate, Butyl Methoxydibenzoylmethane, Helianthus Annuus (Sunflower) Seed Oil, Tocopheryl Acetate, Blue 1, Red 33

Package Label

73549-027-01 30ml